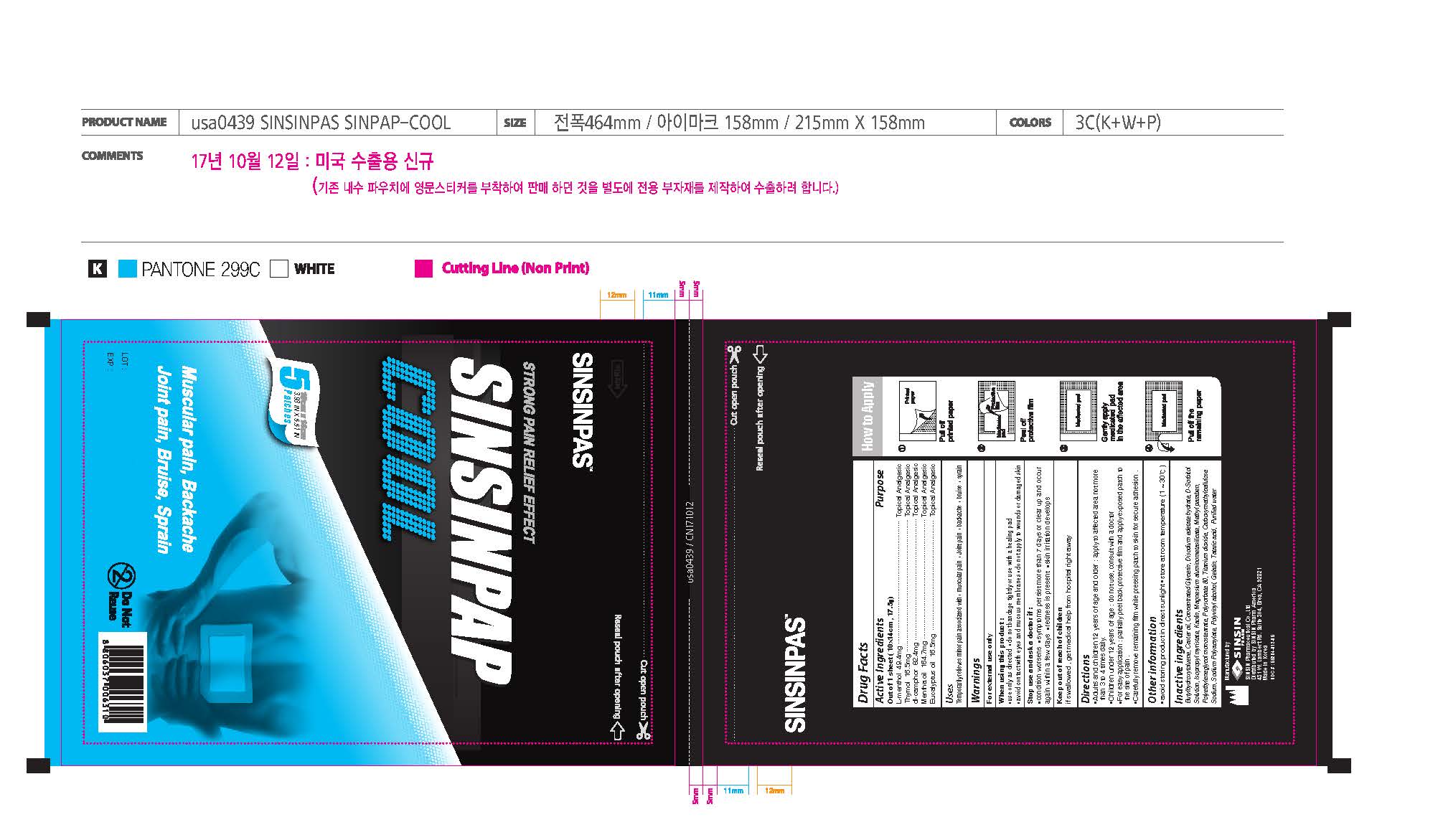 DRUG LABEL: SINSINPAP COOL
NDC: 55264-012 | Form: PATCH
Manufacturer: Sinsin Pharmaceutical Co., Ltd.
Category: otc | Type: HUMAN OTC DRUG LABEL
Date: 20250107

ACTIVE INGREDIENTS: LEVOMENTHOL 49.4 mg/1 1; THYMOL 16.5 mg/1 1; CAMPHOR (SYNTHETIC) 82.4 mg/1 1; PEPPERMINT OIL 164.7 mg/1 1; EUCALYPTUS OIL 16.5 mg/1 1
INACTIVE INGREDIENTS: BUTYLATED HYDROXYTOLUENE; CASTOR OIL; GLYCERIN; EDETATE DISODIUM; SORBITOL; ISOPROPYL MYRISTATE; KAOLIN; SILODRATE; METHYLPARABEN; PEG-4 STEARATE; POLYSORBATE 80; TITANIUM DIOXIDE; CARBOXYMETHYLCELLULOSE SODIUM, UNSPECIFIED FORM; SODIUM POLYACRYLATE (8000 MW); POLYVINYL ALCOHOL, UNSPECIFIED; GELATIN, UNSPECIFIED; TARTARIC ACID; WATER

SINSINPAP COOL

Active ingredients

L-Menthol 49.4 mg

Thymol 16.5 mg

DL-Camphor 82.4 mg

Mentha Oil 164.7 mg

Eucalyptus Oil 16.5 mg

Purpose

Topical Analgesic

Uses

Temporarily relieves minor pain associated with

- muscular pain
- joint pain
- backache
- bruise
- sprain

Warnings

For external use only

When using this product:

- use only as directed
- do not bandage tightly or use with a healing pad
- avoid contact with the eyes and mucous membranes
- do not apply to wounds or damaged skin

Stop use and ask a doctor if

- conditions worsens
- symptoms persist for more than 7 days or clear up and occur again within a few days
- redness is present
- skin irritation develops

Keep out of reach of children.

If swallowed, get medical help from hospital right away

Directions

- Adults and children 12 years of age and over:apply to affected area not more than 3 to 4 times daily.
- Children under 12 years of age:do not use, consult a doctor
- For easy application: partially peel back protective film and apply exposed patch to the site of pain.
- Carefully remove remaining film while pressing patch to skin for secure adhesion.

Storage condition

- avoid storing product in direct sunlight
- store at room temperature

Inactive ingredients

BHT, Castor oil, Concentrated Glycerin, Disodium edetate hydrate, D-sorbitol, Isopropyl myristate, Kaolin, Magnesium aluminometasilicate, Methyl Paraben, PEG-4 stearate, Polysorbate 80, Titanium dioxide, Carboxymethylcellulose Sodium, Sodium Polyacrylate, Polyvinyl alchol, Gelatin, Tataric acid, Purified water

Manufactured by:

SINSIN PHARM. CO., LTD.

Distributed by SS Pharmed USA

Made in Korea

NDC # : 55264-012-01